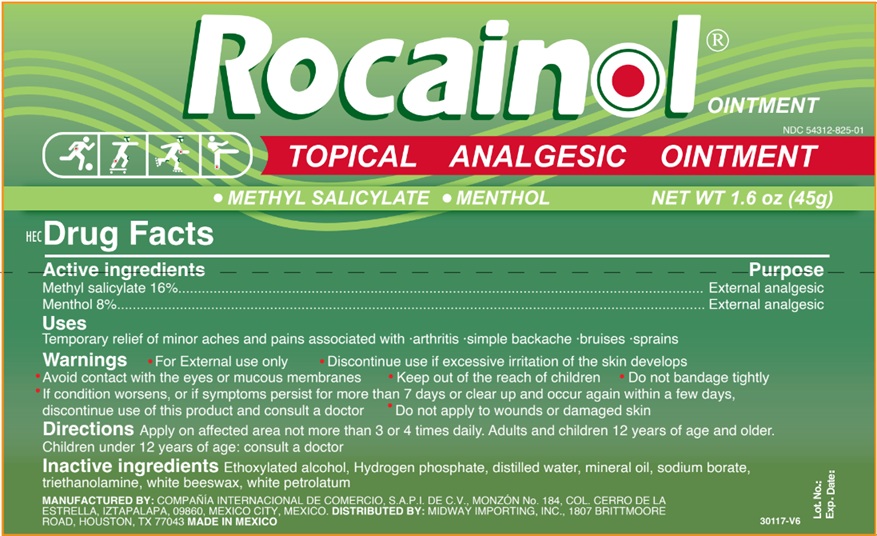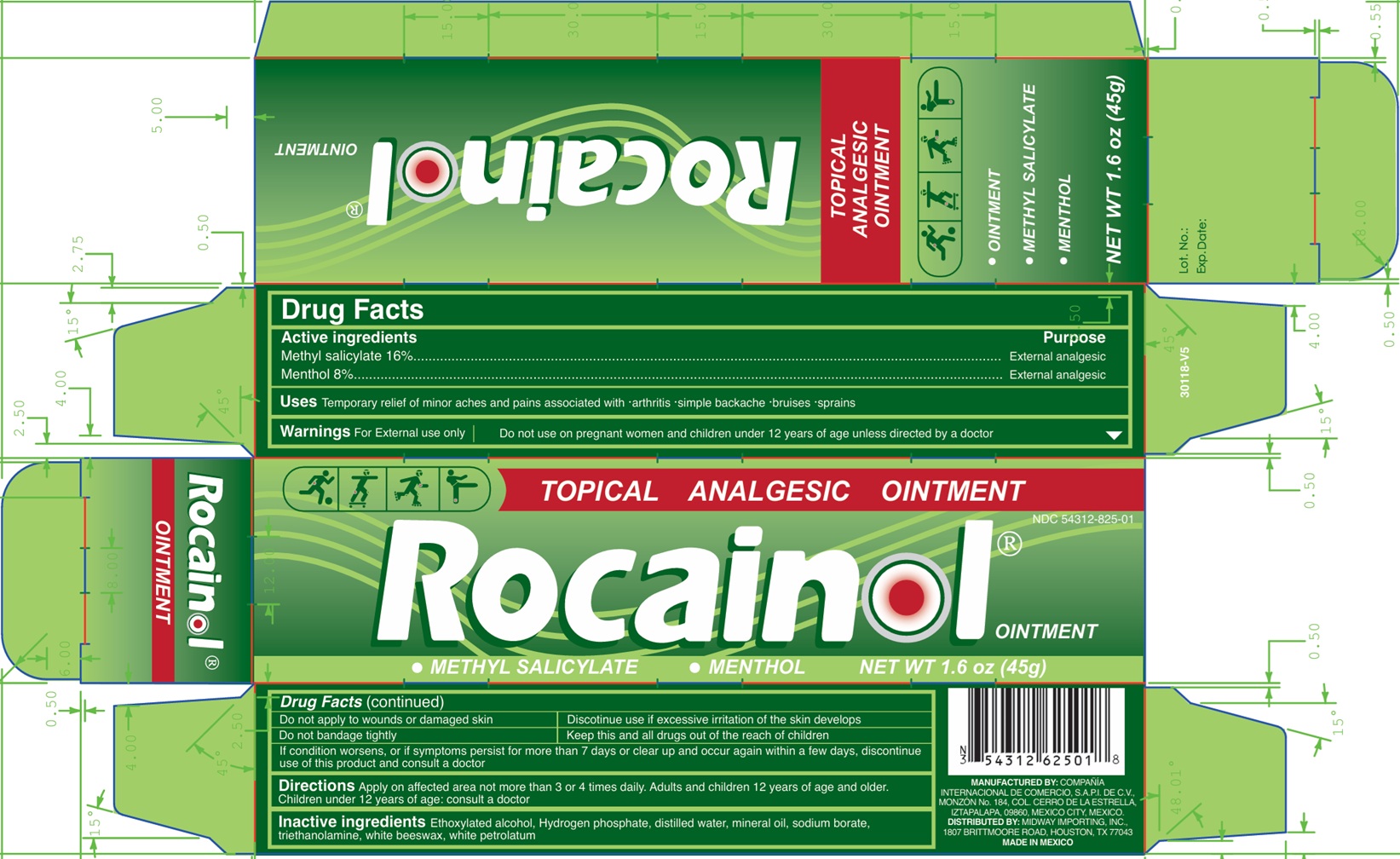 DRUG LABEL: Rocainol TOPICAL ANALGESIC
NDC: 54312-825 | Form: OINTMENT
Manufacturer: Compania Internacional de Comercio, S.A.P.I de C.V.
Category: otc | Type: HUMAN OTC DRUG LABEL
Date: 20250710

ACTIVE INGREDIENTS: METHYL SALICYLATE 16 g/100 g; MENTHOL 8 g/100 g
INACTIVE INGREDIENTS: ALCOHOL; PHOSPHATE ION(2-); WATER; MINERAL OIL; SODIUM BORATE; TROLAMINE; WHITE WAX; PETROLATUM

Rocainol TOPICAL ANALGESIC OINTMENT

Active ingredients

Methyl salicylate 16% Menthol 8%

Purpose

External analgesic

Uses

Temporary relief of minor aches and pains associated with • arthritis • simple backache • bruises • sprains

Warnings

For External use only

Do not use

on pregnant women and children under 12 years of age unless directed by a doctor

Do not apply

to wounds or damaged skin Do not bandage tightly

Discontinue use

if excessive irritation of the skin develops

Keep this and all drugs out of the reach of children.

If condition worsens, or if symptoms persist for more than 7 days or clear up and occur again within a few days, discontinue use of this product and consult a doctor

Directions

Apply on affected area not more than 3 or 4 times daily. Adults and children 12 years of age and older. Children under 12 years of age: consult a doctor

Inactive ingredients

Ethoxylated alcohol, Hydrogen phosphate, distilled water, mineral oil, sodium borate, triethanolamine, white beeswax, white petrolatum